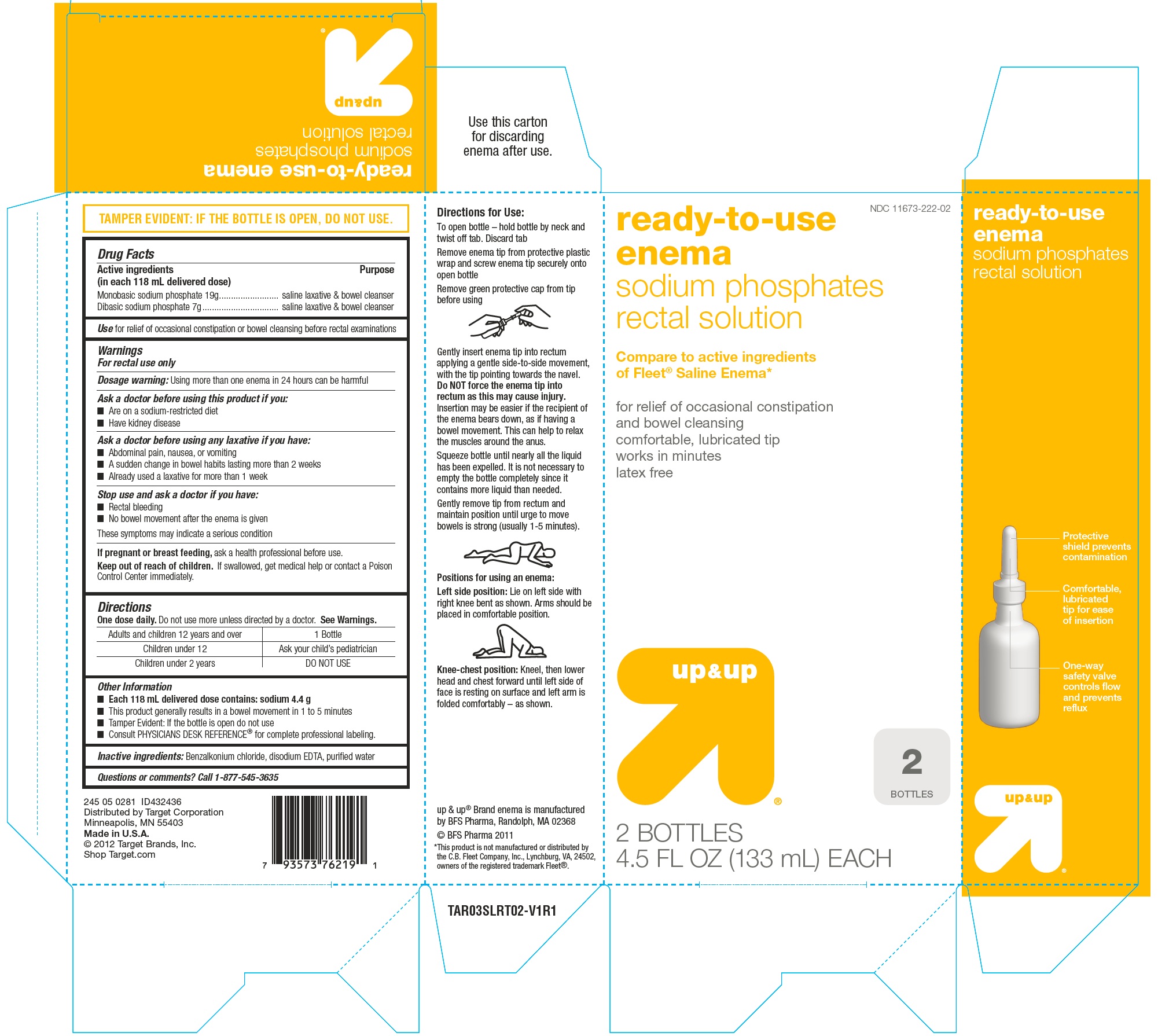 DRUG LABEL: Ready-to-Use Enema
NDC: 11673-222 | Form: ENEMA
Manufacturer: Target Corporation
Category: otc | Type: HUMAN OTC DRUG LABEL
Date: 20120823

ACTIVE INGREDIENTS: SODIUM PHOSPHATE, MONOBASIC 19 g/118 mL; SODIUM PHOSPHATE, DIBASIC 7 g/118 mL
INACTIVE INGREDIENTS: BENZALKONIUM CHLORIDE; EDETATE DISODIUM; WATER

Drug Facts

Active ingredient (in each 118 mL delivered dose)

Sodium Phosphate 19 g

Dibasic Sodium Phosphate 7 g

Purpose

saline laxative & bowel cleanser

Use

for relief of occasional constipation or bowel cleansing before rectal examinations

Warnings

For rectal use only

Dosage warning: Using more than one enema in 24 hours can be harmful

Ask a doctor before using this product if you:

- Are on a sodium-restricted diet
- Have kidney disease

Ask a doctor before using any laxative if you have:

- Abdominal pain, nausea, or vomiting
- A sudden change in bowel habits lasting more than 2 weeks
- Already used a laxative for more than 1 week

Stop use and ask a doctor if you have:

- Rectal bleeding
- No bowel movement after the enema is given

These symptoms may indicate a serious condition

If pregnant or breast-feeding,

ask a health professional before use.

Keep out of reach of children

If swallowed, get medical help or contact a Poison Control Center right away.

When using this product, do not use more than directed.

Serious side effects may occur from excess dosage.

Directions

One dose daily. Do not use more unless directed by a doctor. See Warnings.

adults & children 12 years and older | 1 Bottle
children under 12 years | Ask your child's pediatrician
children under 2 years | DO NOT USE

Other Information

- Each 118 mL contains: sodium 4.4 g
- This product generally results in a bowel movement in 1 to 5 minutes
- Tamper Evident: If the bottle is open do not use
- Consult PHYSICIAN DESK REFERENCE® for complete professional labeling.

Inactive Ingredients

Benzalkonium chloride, disodium EDTA and purified water

Questions or comments?

Call 1-877-545-3635

Principal Display Panel

Principal Package Display